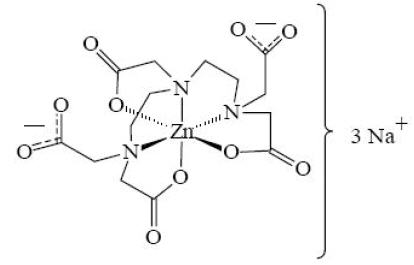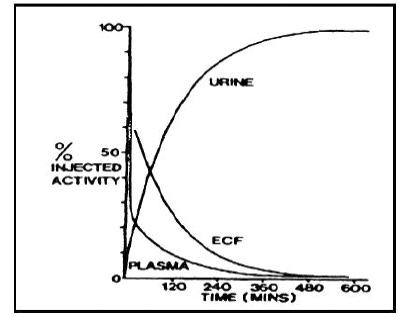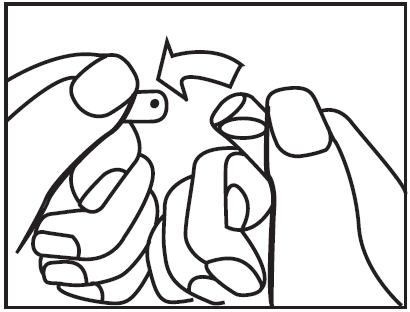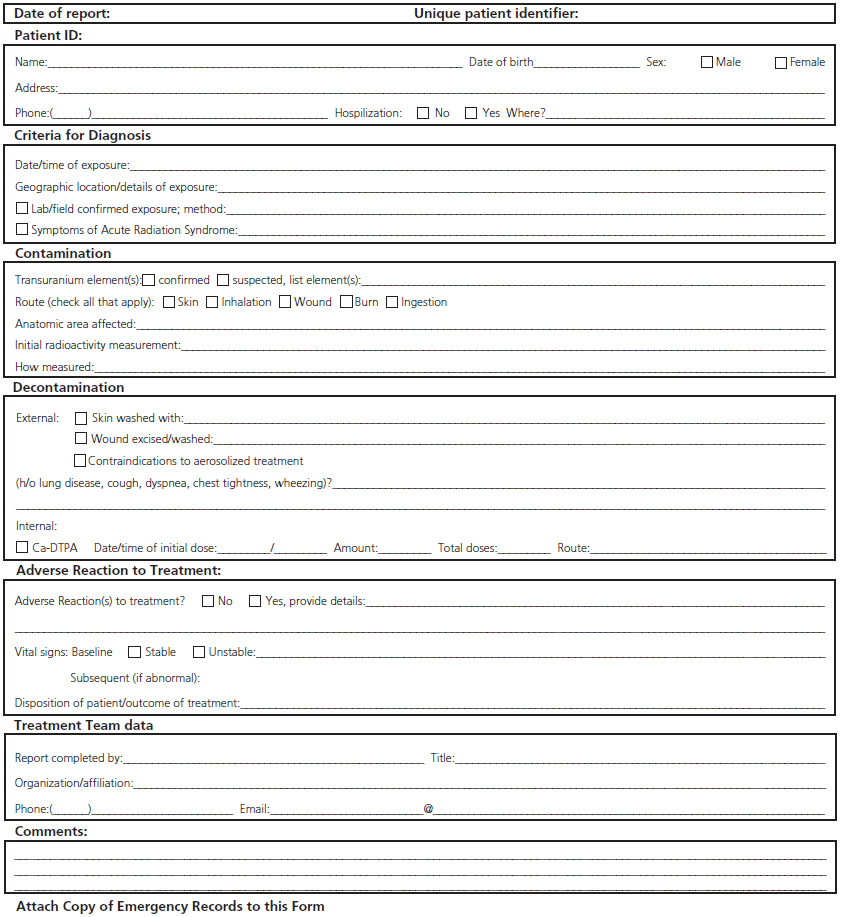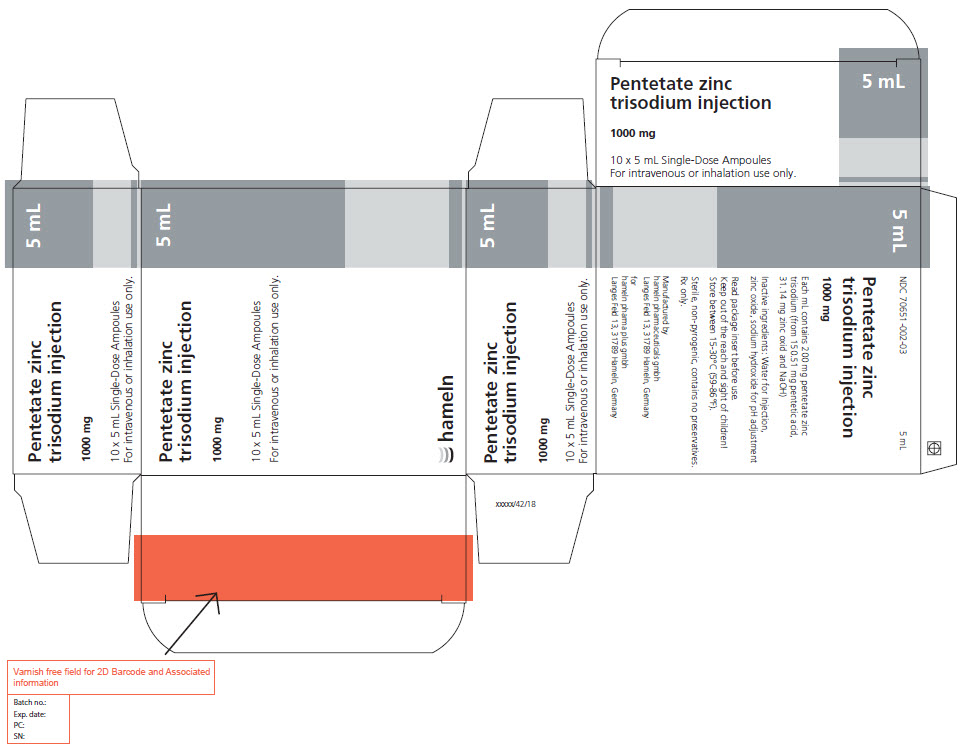 DRUG LABEL: Pentetate zinc trisodium
NDC: 70651-002 | Form: INJECTION, SOLUTION, CONCENTRATE
Manufacturer: hameln pharma gmbh
Category: prescription | Type: HUMAN PRESCRIPTION DRUG LABEL
Date: 20210106

ACTIVE INGREDIENTS: Pentetate zinc trisodium 1000 mg/5 mL
INACTIVE INGREDIENTS: water; Zinc oxide; sodium hydroxide

HIGHLIGHTS OF PRESCRIBING INFORMATION

These highlights do not include all the information needed to use PENTETATE ZINC TRISODIUM INJECTION safely and effectively.
See full prescribing information for PENTETATE ZINC TRISODIUM INJECTION.
Pentetate zinc trisodium injection (Zn-DTPA)
For intravenous or inhalation administration
Initial U.S. Approval: 2004

WARNING: ASTHMA EXACERBATION WITH NEBULIZATION and DEPLETION OF TRACE METALS DURING THERAPY

See full prescribing information for complete boxed warning.

- Nebulized Zn-DTPA may be associated with asthma exacerbation. (5.1)
- Zn-DTPA is associated with depletion of trace metals. The risk for depletion increases when Zn-DTPA is administered over several months. Monitor serum zinc levels, serum creatinine, BUN, electrolytes, urinalysis and blood cell counts during Ca-DTPA or Zn-DTPA therapy. (2.4, 5.2)

1 INDICATIONS AND USAGE

Pentetate zinc trisodium injection is a radiomitigation chelator indicated for treatment of individuals with known or suspected internal contamination with plutonium, americium, or curium to increase the rates of elimination. (1)

2 DOSAGE AND ADMINISTRATION

Chelation treatment is most effective if administered within the first 24 hours. Administer Ca-DTPA, if available, as the initial dose. (2.1, 2.2)

If Ca-DTPA is not available during the first 24 hours,

- in adults and adolescents, administer intravenously a single 1.0 gram Zn-DTPA initial dose. (2.1)
- in children less than 12 years of age, administer intravenously a single 14 mg/kg Zn-DTPA initial dose, not to exceed 1.0 gram. (2.1)

After the first 24 hours, continue chelation therapy with Zn-DTPA:

- in adults and adolescents, administer intravenously 1.0 gram Zn-DTPA once daily. (2.1)
- in children less than 12 years of age, administer intravenously 14 mg/kg Zn-DTPA once daily, not to exceed 1.0 gram daily. (2.1)

See Full Prescribing Information for dose (2.1) and nebulized chelation therapy. (2.3)

3 DOSAGE FORMS AND STRENGTHS

1000 mg / 5 mL single-use ampoules. (3)

4 CONTRAINDICATIONS

None (4)

5 WARNINGS AND PRECAUTIONS

- Nebulized chelation therapy may be associated with exacerbation of asthma. Monitor patients for signs and symptoms of asthma exacerbation when administering Zn-DTPA by the inhalation route. (5.1)
- Zn-DTPA is associated with depletion of endogenous trace metals (e.g., zinc, magnesium, manganese). (5.2)
- Take appropriate safety measures to minimize contamination of care-takers by contaminated body fluids. (5.3)

6 ADVERSE REACTIONS

There is limited experience with Zn-DTPA. Nebulized chelation therapy may be associated with exacerbation of asthma. Headache, light headedness, and pelvic pain have been reported. (6)

To report SUSPECTED ADVERSE REACTIONS, contact the hameln Pharmacovigilance Department at +44 (0) 7706 210 133 or drugsafety@hameln.co.uk or FDA at 1-800-FDA-1088 or www.fda.gov/medwatch.

7 DRUG INTERACTIONS

Adequate and well-controlled drug-drug interaction studies in humans were not identified in the literature. (7)

8 USE IN SPECIFIC POPULATIONS

- Nursing Mothers: Women with known or suspected internal contamination with radiocontaminants should not breast feed, whether or not they are receiving chelation therapy. (8.3)
- Pediatric Use: Safety and effectiveness of intravenous Zn-DTPA were extrapolated from adults. Safety and effectiveness of nebulized route of administration have not been established. (8.4)

FULL PRESCRIBING INFORMATION

WARNING: ASTHMA EXACERBATION WITH NEBULIZATION and DEPLETION OF TRACE METALS DURING THERAPY

- Nebulized Zn-DTPA may be associated with asthma exacerbation. (5.1)
- Zn-DTPA is associated with depletion of trace metals. The risk for depletion increases when Zn-DTPA is administered over several months. Monitor serum zinc levels, serum creatinine, BUN, electrolytes, urinalysis and blood cell counts during Ca-DTPA or Zn-DTPA therapy. (2.4, 5.2)

1 INDICATIONS AND USAGE

Zn-DTPA is indicated for treatment of individuals with known or suspected internal contamination with plutonium, americium, or curium to increase the rates of elimination.

2 DOSAGE AND ADMINISTRATION

2.1 Dose

Administer Ca-DTPA as the initial dose during the first 24 hours after internal contamination. Ca-DTPA is more effective than Zn-DTPA during this time period (see Ca-DTPA labeling). If Ca-DTPA is not available, use Zn-DTPA as initial therapy. On the next day, if additional chelation therapy is indicated, begin daily treatment with Zn-DTPA. If Zn-DTPA is not available, chelation therapy may continue with Ca-DTPA and concomitant mineral supplements containing zinc should be given (see Ca-DTPA labeling).

Do not administer more than one dose per 24 hour period.

If Ca-DTPA is not available during the first 24 hours:

- in adults and adolescents, administer intravenously a single 1.0 gram initial dose of Zn-DTPA.
- in children less than 12 years of age, administer intravenously a single 14 mg/kg initial dose of Zn-DTPA, not to exceed 1.0 gram.

After the first 24 hours, continue chelation therapy with Zn-DTPA:

- in adults and adolescents, administer intravenously 1.0 gram Zn-DTPA once daily.
- in children less than 12 years of age, administer intravenously 14 mg/kg Zn-DTPA once daily, not to exceed 1.0 gram daily.

Renally Impaired Patients

No dose adjustment is needed. However, renal impairment may reduce the rate at which chelators remove radiocontaminants from the body. In heavily contaminated patients with renal impairment, dialysis may be used to increase the rate of elimination. High efficiency high flux dialysis is recommended. Because dialysis fluid will become radioactive, radiation precautions must be taken to protect personnel, other patients, and the general public.

2.2 General

Chelation treatment is most effective if administered within the first 24 hours after internal contamination. Start chelation treatment as soon as possible after suspected or known internal contamination. When treatment cannot be started right away, give chelation treatment as soon as it becomes available. Chelation treatment is still effective even after time has elapsed following internal contamination. The chelating effects of Zn-DTPA are greatest when the radiocontaminants are still circulating or are in interstitial fluids. The effectiveness of chelation decreases with time following internal contamination as the radiocontaminants become sequestered in liver and bone.

If internal contamination with radiocontaminants other than plutonium, americium, or curium, or unknown radiocontaminants is suspected, additional therapies may be needed (e.g., Prussian blue, potassium iodide).

2.3 Methods of Administration

Use intravenous administration of Zn-DTPA if the route of internal contamination is not known or if multiple routes of internal contamination are likely. Administer Zn-DTPA solution (1 gram in 5 mL) either with a slow intravenous push over a period of 3-4 minutes or by intravenous infusion over 30 minutes diluted in 100-250 mL of 5% dextrose in water (D5W), Ringers Lactate, or Normal Saline.

In individuals whose internal contamination is only by inhalation, Zn-DTPA can be administered by nebulized inhalation as an alternative route of administration.

Dilute Zn-DTPA for nebulization at a 1:1 ratio with sterile water or saline. After nebulization, encourage patients to avoid swallowing any expectorant. Some individuals may experience respiratory adverse events after inhalation therapy. [See Warnings and Precautions (5.1)] The safety and effectiveness of the nebulized route of administration have not been established in the pediatric population.

The safety and effectiveness of the intramuscular route of injection have not been established.

2.4 Monitoring

When possible, obtain baseline blood and urine samples (CBC with differential, BUN, serum chemistries and electrolytes, urinalysis and blood and urine radioassays) before initiating treatment.

To establish an elimination curve, obtain a quantitative baseline estimate of the total internalized transuranium element(s) and measures of elimination of radioactivity by appropriate whole-body counting, by bioassay (e.g., biodosimetry), or fecal/urine sample whenever possible.

During Treatment

- Measure the radioactivity in blood, urine, and fecal samples weekly to monitor the radioactive contaminant elimination rate.
- Monitor CBC with differential, BUN, serum creatinine and electrolytes, and urinalysis measurements.
- Record any adverse events from Zn-DTPA.

3 DOSAGE FORMS AND STRENGTHS

1000 mg / 5 mL single-use ampoules.

4 CONTRAINDICATIONS

None.

5 WARNINGS AND PRECAUTIONS

5.1 Asthma Exacerbation

Nebulized chelation therapy is associated with asthma exacerbation. Monitor patients for signs and symptoms of asthma exacerbation when administering Zn-DTPA by the inhalation route. [See Adverse Reactions (6)]

5.2 Depletion of Body Trace Mineral Stores

Zn-DTPA treatment may lead to depletion of body stores of endogenous metals (e.g. magnesium, manganese). The risk for depletion increases when Zn-DTPA is administered over several months. Monitor serum zinc levels, electrolytes and blood cell counts during Ca-DTPA or Zn-DTPA therapy. Give mineral or vitamin plus mineral supplements as appropriate. [See Dosage and Administration (2.4)]

5.3 Risks to Care-takers

Radioactive metals are known to be excreted in the urine, feces, and breast milk. In individuals with recent internal contamination with plutonium, americium, or curium, Zn-DTPA treatment increases excretion of radioactivity in the urine. Take appropriate safety measures to minimize contamination of others. [See Patient Counseling Information (17)]

6 ADVERSE REACTIONS

In the U.S. Registry, a total of 646 individuals received at least one dose of either Ca-DTPA or Zn-DTPA. Of these, 62 received Zn-DTPA by one or more routes of administration. Forty-eight individuals were dosed by intravenous administration, 18 by inhalation and 8 by other or unknown routes of administration.

Of the individuals that received Zn-DTPA, 23/62 (37%) received one dose and 8 (13%) received two doses. The remaining 31 individuals received three or more doses. The largest number of Zn-DTPA doses to a single individual was 574 doses delivered over 3.5 years.

Overall, the presence or absence of adverse events was recorded in 310/646 individuals. Of these 19 (6.1%) individuals reported at least one adverse event. The total number of recorded adverse events was 20. Of the 20 adverse events, 1 individual treated with Zn-DTPA reported headache, lightheadedness, and pelvic pain.

Two individuals experienced cough and/or wheezing with nebulized Ca-DTPA therapy however there was no report of such events with nebulized Zn-DTPA.

7 DRUG INTERACTIONS

Adequate and well-controlled drug-drug interaction studies in humans were not identified in the literature. When an individual is contaminated with multiple radiocontaminants, or when the radiocontaminants are unknown, additional therapies may be needed (e.g., Prussian blue, potassium iodide).

8 USE IN SPECIFIC POPULATIONS

8.1 Pregnancy

TERATOGENIC EFFECTS

Pregnancy Category B

Risk Summary

There are no adequate and well-controlled studies of Zn-DTPA use in pregnant women. Chelation treatment of pregnant women should begin and continue with Zn-DTPA. Reproduction studies have been performed in pregnant mice at doses up to 31 times (11.5 mmol/kg) the recommended daily human dose and have revealed no evidence of impaired fertility or harm to the fetus due to Zn-DTPA. There was a slight reduction in the average birth weight. Because animal reproduction studies are not always predictive of human response, this drug should be used during pregnancy only if clearly needed.

8.3 Nursing mothers

It is not known whether Zn-DTPA is excreted in human milk. Radiocontaminants are known to be excreted in breast milk. Women with known or suspected internal contamination with radiocontaminants should not breast feed, whether or not they are receiving chelation therapy. Precautions should be taken when discarding breast milk. [See Warnings and Precautions (5.3)]

8.4 Pediatric use

The safety and effectiveness of Zn-DTPA were established in the adult population and efficacy was extrapolated to the pediatric population for the intravenous route based on the comparability of pathophysiologic mechanisms. The dose is based on body size adjustment for an intravenous drug that is renally cleared [See Dosage and Administration (2.1)]. The safety and effectiveness of the nebulized route of administration have not been established in the pediatric population.

10 OVERDOSAGE

Overdose with Zn-DTPA has not been reported.

11 DESCRIPTION

Pentetate zinc trisodium injection contains the sodium salt of zinc diethylenetriaminepentaacetate. Pentetate zinc trisodium is also known as trisodium zinc diethylenetriaminepentaacetate and is commonly referred to as Zn-DTPA. It has a molecular formula of Na3ZnC14H18N3O10 and a molecular weight of 522.7 Daltons. It is represented by the following structural formula:

Zn-DTPA is supplied as a clear, colorless, hyperosmolar (1260 mOsmol/kg) solution in a colorless ampoule containing 5 mL. The ampoule contents are sterile, non-pyrogenic and suitable for intravenous administration. Each mL of solution contains the equivalent of 200 mg pentetate zinc trisodium (obtained from 150.51 mg pentetic acid, 31.14 mg zinc oxide and NaOH) and water for injection, USP. The pH of the solution is adjusted with NaOH and is between 6.5-7.5.

12 CLINICAL PHARMACOLOGY

12.1 Mechanism of Action

Zn-DTPA forms stable chelates with metal ions by exchanging zinc for a metal of greater binding capacity. The radioactive chelates are then excreted by glomerular filtration into the urine. In animal studies, Zn-DTPA forms less stable chelates with uranium and neptunium in vivo resulting in deposition of these elements in tissues including the bone. Zn-DTPA treatments are not expected to be effective for uranium and neptunium. Radioactive iodine is not bound by DTPA.

12.2 Pharmacodynamics

In a study of rodents internally contaminated with plutonium, the rate of plutonium elimination was measured after treatment with Ca-DTPA and Zn-DTPA given intravenously as a single dose of 10 to 1,000 micromol/kg (0.54-54 × maximum human dose, MHD). When treated within one hour of internal contamination, Ca-DTPA resulted in about a 10 fold higher rate of elimination of plutonium in the urine as compared to Zn-DTPA. The chelating capacity of Ca-DTPA is greatest immediately and up to approximately 24 hours after internal contamination when the radiocontaminant is still circulating and readily available for chelation. After the first dose of Ca-DTPA, maintenance treatment with either Ca-DTPA or Zn-DTPA resulted in similar rates of elimination of radioactivity. However, at comparable doses, Zn-DTPA had less toxicity (e.g., less depletion of trace metals, lower rate of mortality, the absence of kidney and liver vacuolization, and absence of small bowel hemorrhagic lesions).

In another study, rodents contaminated with aerosolized plutonium and americium were treated with Ca-DTPA and Zn-DTPA. The treatment schedule involved inhalation of Ca-DTPA 2 micromol/kg (0.11 MHD) 30 minutes after contamination followed by inhalation of Zn-DTPA 2 micromol/kg at approximately 6 hours, 1, 2, 3, and 6 days, then twice weekly to day 26 or day 27. The treatment regime reduced the lung deposit of plutonium and americium to 1-2% of that in untreated animals. Systemic deposit in liver and skeleton were reduced by half.

Literature and U.S. Registry data in humans indicate that intravenous administration of Zn-DTPA forms chelates with radioactive contaminants found in the circulation, interstitial fluid, and tissues. When Zn-DTPA is administered by inhalation, it can chelate transuranium elements. Expectoration is expected to decrease the amount of radioactive contaminant available for systemic absorption.

The effectiveness of chelation decreases with time after internal contamination because the transuranium elements become incorporated into the tissues. Give chelation treatment as soon as possible after known or suspected internal contamination with transuranium elements has occurred. [See Dosage and Administration (2.1, 2.2)]

12.3 Pharmacokinetics

Plasma retention and urinary excretion data were obtained in 2 subjects that received 750 kBq of ^14C-DTPA. As shown in Figure 1, the radiolabeled DTPA was rapidly distributed throughout the extracellular fluid space and was cleared by glomerular filtration. The plasma retention up to 7 hours post dosing was expressed by the sum of three exponential components with average half lives of 1.4 min, 14.5 min, and 94.4 min. The level of activity in the plasma was below the limit of detection 24 hours after injection. During the study, no detectable activity was exhaled or excreted in the feces. By 24 hours, cumulative urinary excretion was more than 99% of the injected dose.

Figure 1: Percent of ^14C-DTPA Distribution

Absorption

Zn-DTPA is poorly absorbed in the gastrointestinal tract. In animal studies, after oral administration, absorption was approximately 5%. In a U.S. Registry of 18 patients who received a single inhaled or intravenous dose of 1 gram, urine data indicate that the inhaled product was absorbed and resulted in a comparable elimination of the radiocontaminant. One study of 2 human subjects that received Ca-DTPA with ^14C-DTPA by inhalation revealed approximately 20% absorption from the lungs. Human or animal bioavailability comparisons for Zn-DTPA are not available after administration by inhalation and intravenous injection. [See Clinical Studies (14)]

Distribution

Following intravenous administration, Zn-DTPA is rapidly distributed throughout the extracellular fluid space. No significant amount of Zn-DTPA penetrates into erythrocytes or other cells. No accumulation of Zn-DTPA in specific organs has been observed. There is little or no binding of the chelating agent by the renal parenchyma.

Metabolism

Zn-DTPA undergoes a minimal amount of metabolic change in the body.

Adverse Metabolic Effects

Zn-DTPA results in minimal depletion of magnesium and manganese.

Elimination

Zn-DTPA is cleared from the plasma in the first few hours after dosing through urinary excretion by glomerular filtration. Renal tubular excretion has not been documented. In stool samples, only a very small amount of radioactivity (<3%) was detected.

Renal Impaired and/or Compromised Liver Function Patients

Adequate and well-controlled pharmacokinetic and pharmacodynamic studies in renally impaired and/or hepatically impaired patients were not identified in the literature. Both Zn-DTPA and its radioactive chelates are excreted by glomerular filtration. Impaired renal function may decrease their rates of elimination and increase the serum half-life of Zn-DTPA.

13 NONCLINICAL TOXICOLOGY

13.1 Carcinogenesis, Mutagenesis, Impairment of Fertility

Studies with Zn-DTPA to evaluate carcinogenesis, mutagenesis and impairment of fertility have not been performed. Data for Zn-DTPA effects on spermatogenesis are not available.

13.2 Animal Toxicology and/or Pharmacology

[See Clinical Pharmacology (12)]

14 CLINICAL STUDIES

All clinical data has come from the treatment of individuals who were accidentally contaminated. Observational data were maintained in a U.S. Registry of individuals with internal radiation contamination primarily from acute occupational contamination with plutonium, americium and curium.

In 286 individuals, bioassays were available to measure urinary radioactivity elimination after chelation therapy. Of these 286 individuals, 18 had matched pre- and post-chelator urine radioactivity bioassay results available. The majority of these individuals received Ca-DTPA as the initial component to their chelation therapy. When multiple chelator doses were administered over days, the standard of practice was to switch therapy to Zn-DTPA following an initial dose of Ca-DTPA. Although both chelators were considered equipotent 24 hours following internal contamination, Zn-DTPA was considered less toxic. In one individual who received 3 doses, 1 gram each, by nebulization (1:1 Zn-DTPA and saline) followed by 6 intravenous doses, the urinary excretion of plutonium after the first nebulized dose was increased by a factor of 45.

After initial treatment with Ca-DTPA, maintenance treatment was continued with daily 1 gram Zn-DTPA doses administered over a period of days, months or years, depending on the extent of internal contamination and individual response to therapy. Treatment was generally continued until the excretion enhancement factor (EEF) approached 1. The longest treatment duration was 3.5 years. Similar increases in urinary radioactivity elimination were supported by data from the remaining 268 individuals in the U.S. Registry and from the literature.

16 HOW SUPPLIED

Zn-DTPA is supplied as a sterile solution in 5 mL single-use clear glass ampoules at a concentration of 200 mg/mL for intravenous use. Each ampoule contains the equivalent of 1000 mg of pentetate zinc trisodium.

NDC 70651-002-03: 5 mL single-dose ampoules, package of 10

16.2 Storage

Store between 15-30°C (59-86°F).

16.3 Handling

Inspect parenteral drug products visually for particulate matter and discoloration prior to administration, whenever solution and container permit. The product may be filtered using a sterile filter if particles are seen subsequent to opening of the ampoule.

OPC ampoule: to open, turn so that the point faces upward and break off the neck with a downward movement.

17 PATIENT COUNSELING INFORMATION

Instruct patients to:

- drink plenty of fluids and void frequently to promote dilution of the radioactive chelate in the urine and minimize radiation exposure directly to the bladder.
- use a toilet instead of a urinal, and flush several times after each use.
- clean up spilled urine or feces completely and wash hands thoroughly. Wash clothing or linens separately if blood or urine comes in contact.
- dispose of any expectorant carefully. Avoid swallowing the expectorant if possible.

IInstruct parents and child-care givers to take extra precaution in handling the urine, feces, and expectorants of children to avoid any additional exposure to either the care-giver or to the child.

Instruct nursing mothers to take extra precaution in disposing of breast milk. [See Use in Specific Populations (8.3)]

18 COLLECTION OF PATIENT TREATMENT DATA

To develop long-term response data and information on the risk of developing late malignancy, detailed information on patient treatment should be provided to the manufacturer (see Patient Treatment Data Form). To obtain additional forms, please use the enclosed form as a template or see the following website: www.zn-dtpa.com. These data should include a record of the radioactive body burden and bioassay results at defined time intervals, a description of measurement methods to facilitate analysis of data, and adverse events.

Questions regarding the use of Zn-DTPA for the treatment of internal contamination with transuranium elements may be referred to:

hameln pharmaceuticals ltd
Nexus
Gloucester Business Park
Gloucester, GL3 4AG
United Kingdom
Tel: + 44 / 1452 / 621661
Fax: +44 / 1452 / 632732
e-mail: drugsafety@hameln.co.uk

Contact person: Richard Wysocki
Phone: +44 / 1452 / 621661
Fax: +44 / 1452 / 632732
Email: r.wysocki@hameln.co.uk

Revised: 10/2016

44640/17/16

Zn-DTPA

Patient treatment Data

Send to: hameln pharmaceuticals ltd, Nexus, Gloucester Business Park, Gloucester, GL3 4AG, United Kingdom

PRINCIPAL DISPLAY PANEL - 5 mL Ampoule Package

Pentetate zinc
trisodium injection

1000 mg

10 x 5 mL Single-Dose Ampoules
For intravenous or inhalation use only.

hameln

5 mL